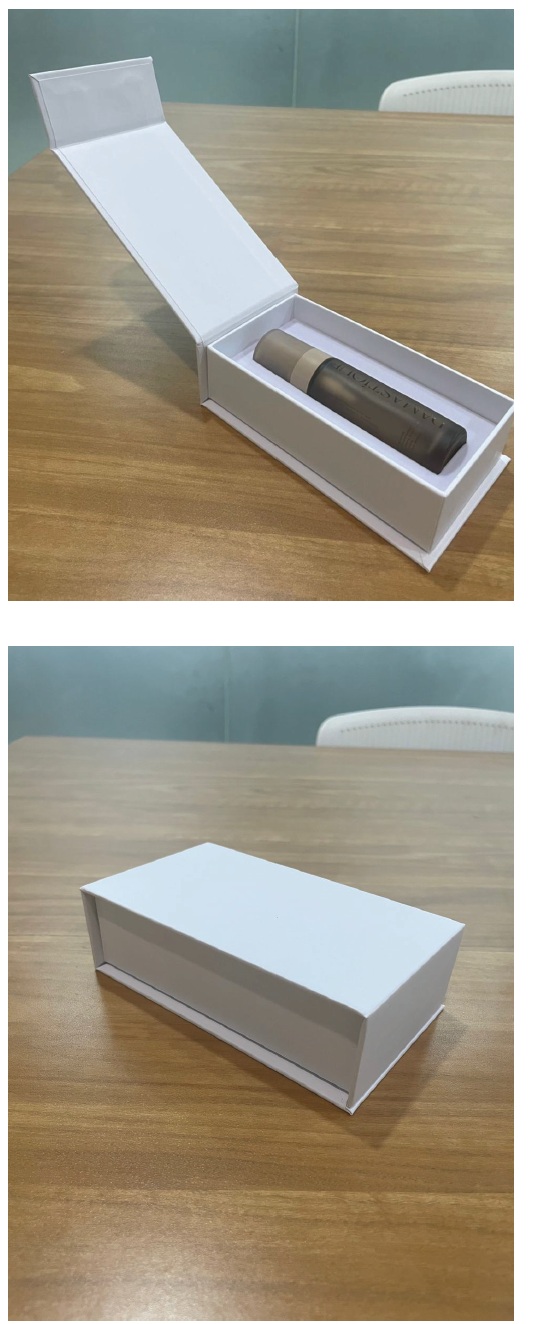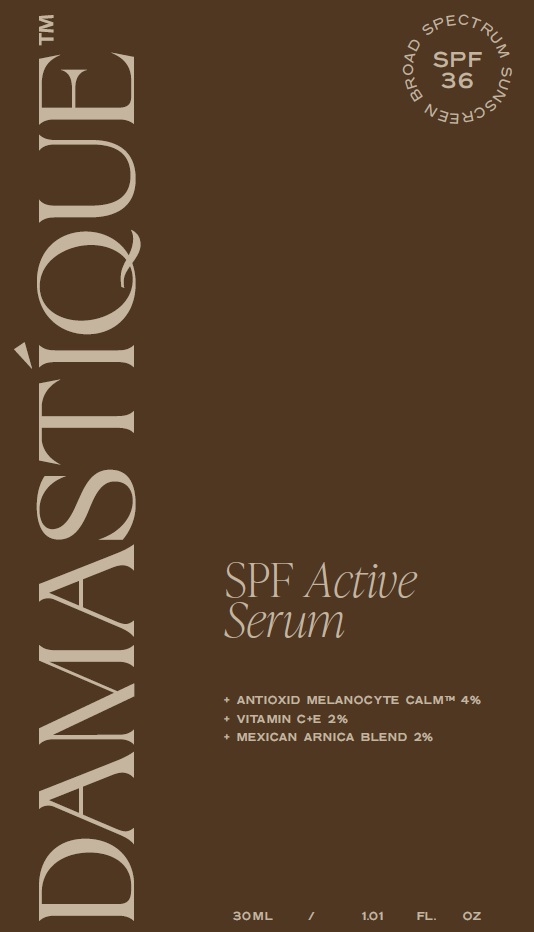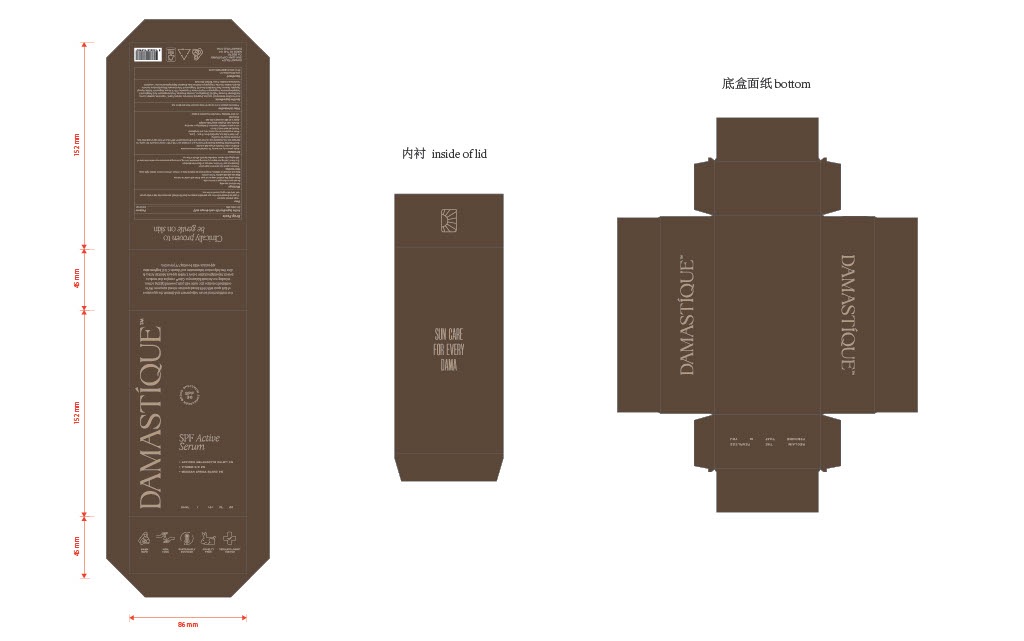 DRUG LABEL: Damastique SPF Active Serum SPF 36
NDC: 87035-027 | Form: EMULSION
Manufacturer: Damastíque
Category: otc | Type: HUMAN OTC DRUG LABEL
Date: 20250822

ACTIVE INGREDIENTS: ZINC OXIDE 200 mg/1 mL
INACTIVE INGREDIENTS: ALOE VERA LEAF JUICE; DICAPRYLYL CARBONATE; MEDIUM-CHAIN TRIGLYCERIDES; ISOAMYL LAURATE; ACAI OIL; ETHOXYDIGLYCOL; ASCORBYL GLUCOSIDE; POLYGLYCERYL-6 POLYRICINOLEATE; PROPANEDIOL; C13-15 ALKANE; MAGNESIUM SULFATE, UNSPECIFIED FORM; GLYCERYL MONOCAPRYLATE; CARAMEL; PASSIFLORA EDULIS SEED OIL; DISTEARDIMONIUM HECTORITE; GLYCERIN; SODIUM CHLORIDE; LEVOMENOL; CAPRYLHYDROXAMIC ACID; TOCOPHEROL; HETEROTHECA INULOIDES FLOWER; CITRIC ACID MONOHYDRATE

Damastique SPF Active Serum SPF 36

Active Ingredient (in each dosage unit)

Zinc Oxide 20%

Purpose

Sunscreen

Uses

• Helps prevent sunburn
• If used as directed with other sun protection measures (see Directions), decreases the risk of skin cancer and early skin aging caused by the sun.

Warnings

For external use only.

Do not use

on damaged or broken skin.

When using this product

keep out of eyes. Rinse with water to remove.

Stop use and ask a doctor

if rash occurs.

Keep out or reach of children.

If swallowed, get medical help or contact a Poison Control Center right away.

Other warnings

• Perform a patch test before full application
• Discontinue use if irritation, redness, or discomfort develops
• Sun Alert: Limiting sun exposure, wearing protective clothing, and using sunscreens may reduce the risks of skin aging, skin cancer, and other harmful effects of the sun.

Directions

• Apply generously and evenly 15 minutes before sun exposure.
• Children under 6 months of age: Ask a doctor.
• Sun Protection Measure:Spending time in the sun increases your risk of skin cancer and early skin aging. To decrease this risk, regularly use a sunscreen with a Broad Spectrum SPF value of 15 or higher and other sun protection measures including:
• Limit time in the sun, especially from 10 a.m. – 2 p.m.
• Wear long-sleeved shirts, pants, hats, and sunglasses
• Reapply at least every 2 hours
• Use a water-resistant sunscreen if swimming or sweating
• Store in cool, dry place away from sunlight
• Apply to all skin exposed to the sun
• Shake well
• Use after applying moisturizer, but before makeup

Other Information

• Protect the product in this container from excessive heat and direct sun

Inactive Ingredients:

Aloe Vera (Aloe Barbadensis) leaf juice, Zinc Oxide, Dicaprylyl Carbonate, Caprylic/Capric Triglyceride, Isoamyl Laurate, Acai (Euterpe Oleracea Fruit) oil, Ethoxydiglycol, Ascorbyl Glucoside, Polyhydroxystearic Acid, Polyglyceryl-6 Polyhydroxystearate, Polyglyceryl-6 Polyricinoleate, Propanediol, C13-15 Alkane, Magnesium Sulfate, Glyceryl Caprylate, Caramel, Passiflora Edulis Seed Oil, Polyglyceryl-3 Polyricinoleate, Disteardimonium Hectorite, Glycerin, Sodium Chloride, Polyglyceryl-6 Xanthan Gum, Bisabolol, Caprylhydroxamic Acid, Tocopherol, Heterotheca Inuloides Flower Extract, Citric Acid.

Questions?

www.damastique.com Email: suncare@damastique.com